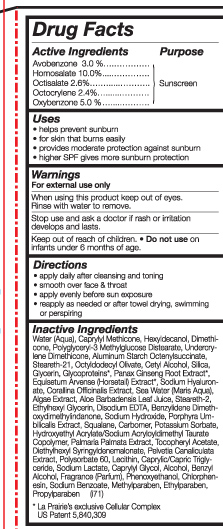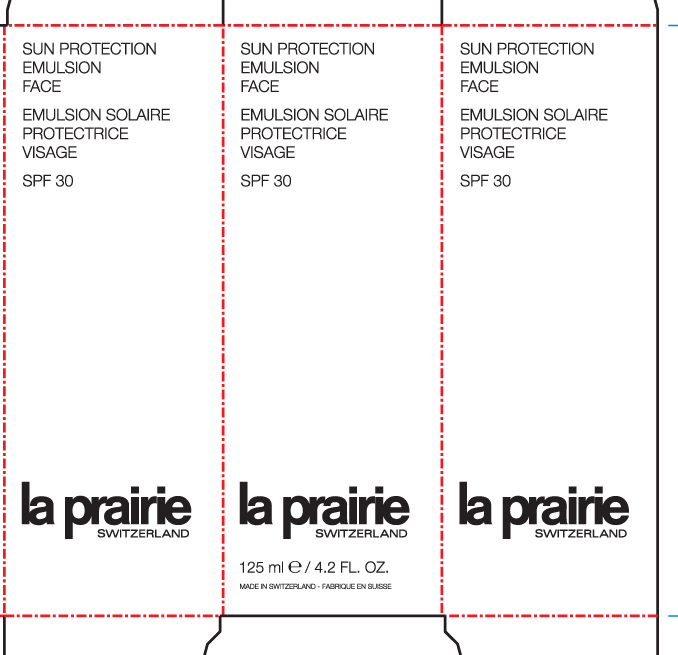 DRUG LABEL: Sun Protection Emulsion  Face 
NDC: 59614-221 | Form: CREAM
Manufacturer: Juvena GMBH
Category: otc | Type: HUMAN OTC DRUG LABEL
Date: 20110214

ACTIVE INGREDIENTS: Avobenzone 3 mL/100 mL; Homosalate 10 mL/100 mL; Octisalate  2.5 mL/100 mL; Octocrylene 2.4 mL/100 mL; Oxybenzone  5 mL/100 mL
INACTIVE INGREDIENTS: Hexyldecanol ; Dimethicone; ALUMINUM STARCH OCTENYLSUCCINATE; STEARETH-21; CETYL ALCOHOL; SILICON DIOXIDE; GLYCERIN; ALOE VERA LEAF; STEARETH-2; EDETATE DISODIUM; SODIUM HYDROXIDE; squalane; POTASSIUM SORBATE; POLYSORBATE 60; MEDIUM-CHAIN TRIGLYCERIDES; SODIUM LACTATE; CAPRYLYL GLYCOL; alcohol; BENZYL ALCOHOL; PHENOXYETHANOL; CHLORPHENESIN; SODIUM BENZOATE; METHYLPARABEN; ETHYLPARABEN; PROPYLPARABEN

Sun Protection Emulsion Face SPF 30

Active Ingredients Purpose

Avobenzone 3.0% sunscreen

Homosalate 10.0% sunscreen

Octisalate 2.6% sunscreen

octocrylene 2.4% sunscreen

Oxybenzone 5.0% sunscreen

PURPOSE

- Helps prevent sunburn

- for skin that burns easily

-provides moderate protection against sunburn

-higher SPF gives more sunburn protection

Keep out of reach of children.
Do not use on infants under 6 months of age.

Stop use and ask a doctor if rash or irritation develops and lasts.

when using this product keep out of eyes.

rinse with water to remove.

DOSAGE AND ADMINISTRATION

Apply daily after cleansing and toning .

Smooth over face and throat.

Apply evenly before sun exposure.

Reapply as needed or after towel drying, swimming or perspiring.

INACTIVE INGREDIENT

Water (Aqua), Caprylyl Methicone, Hexyldecanol, Dimethicone, Polyglyceryl-3 Methylglucose Distearate, Undercrylene Dimethicone, Aluminum Starch Octenylsuccinate, Steareth-21, Octyldodecyl Olivate, Cetyl Alcohol, Silica, Glycerin, Glycoproteins, Panax Ginseng Root Extract*, Equisetum Arvense (Horsetail) Extract*, Sodium Hyaluronate, Corallina Officinalis Extract, Sea Water (Maris Aqua), Algae Extract, Aloe Barbadensis Leaf Juice, Steareth-2, Ethylhexyl Glycerin, Disodium EDTA, Benzylidene Dimethoxydimethylindanone, sodium hydroxide, porphyra Umbilicalis Extract, Squalane, Carbomer, Potassium Sorbate, Hydroxyethyl acrylate/ Sodium Acryloyldimethyl Taurate Copolymer, Palmaria Pakmata Extract, Tocopheryl Acetate, Diethylhexyl Syringyldenemalonate, Pelvetia Canaliculata Extract, Polysorbate 60, Lecithin, Caprylic/ Capric Triglyceride, Sodium Lactate, Caprylyl Glycol, Alcohol, Benzyl Alcohol, Fragrance (parfum), Phenoxyethanol, Chlorphenesin, Sodium Benzoate, Methylparaben, Ethylparaben, Propyparaben

PACKAGE LABEL

Sun protection emulsion face SPF 30
125mL/ 4.2 FL. OZ.